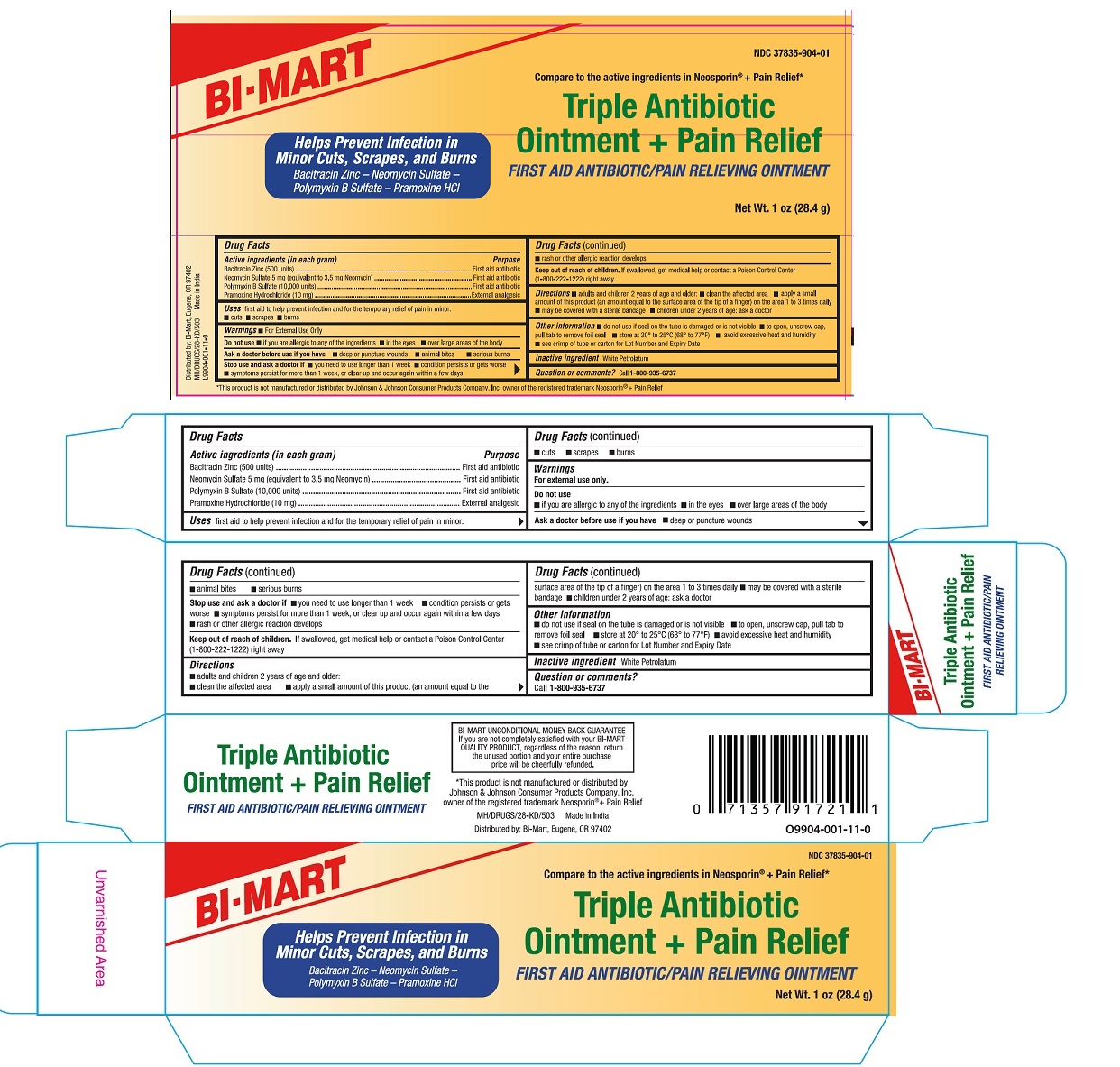 DRUG LABEL: Triple Antibiotic Plus Pain Relief
NDC: 37835-904 | Form: OINTMENT
Manufacturer: Bi-Mart
Category: otc | Type: HUMAN OTC DRUG LABEL
Date: 20251004

ACTIVE INGREDIENTS: BACITRACIN ZINC 400 [USP'U]/1 g; NEOMYCIN SULFATE 5 mg/1 g; POLYMYXIN B SULFATE 10000 [USP'U]/1 g; PRAMOXINE HYDROCHLORIDE 10 mg/1 g
INACTIVE INGREDIENTS: WHITE PETROLATUM

Active Ingredients (in each gram)

Bacitracin Zinc 400 units

Neomycin Sulfate 5 mg (equivalent to 3.5 mg Neomycin)

Polymyxin B Sulfate 10000 units

Pramoxine Hydrochloride 10 mg

Purposes

First aid antibiotic

First aid antibiotic

First aid antibiotic

External analgesic

Uses

first aid to help prevent infection and for the temporary relief of pain in minor:

- cuts
- scrapes
- burns

Warnings

- For External Use Only

Do not use

- if you are allergic to any of the ingredients
- in the eyes
- over large areas of the body

Ask a doctor before use if you have

- deep or puncture wounds
- animal bites
- serious burns

Stop use and ask a doctor if

- you need to use longer than 1 week
- condition persists or gets worse
- symptoms persist for more than 1 week, or clear up and occur again within a few day
- a rash or other allergic reaction develops

Keep out of reach of children.If swallowed, get medical help or contact a Poison Control Center (1-800-222-1222) right away.

Directions

Adults and children 2 years of age and older

- clean affected area
- apply a small amount of this product (an amount equal to the surface area of the tip of a finger) on the area 1 to 3 times daily
- may be covered with a sterile bandage

Children under 2 years of age:ask a doctor

Other information

- do not use if seal on the tube is damaged or is not visible.
- to open, unscrew cap, pull tab to remove foil seal.
- Store at 20° to 25°C (68° to 77°F)
- avoid excessive heat and humidity
- see crimp of tube or carton for Lot Number and Expiry Date

Inactive ingredient

White Petrolatum

Questions or comments?

Call 1-800-935-6737

Principal Display Panel

NDC 37835-904-01

Triple Antibiotic Ointment + Pain Relief

First Aid Antibiotic/Pain Relieving Ointment

Compare to the Active Ingredients in Neosporin®+ Pain Relief*

*This product is not manufactured or distributed by Johnson & Johnson Corporation Products Company, Inc, owner of the registered trademark Neosporin®+ Pain Relief .

Net. Wt. 1 oz (28.4 g)

Distributed by:

Bi-Mart

Eugene, OR 97402